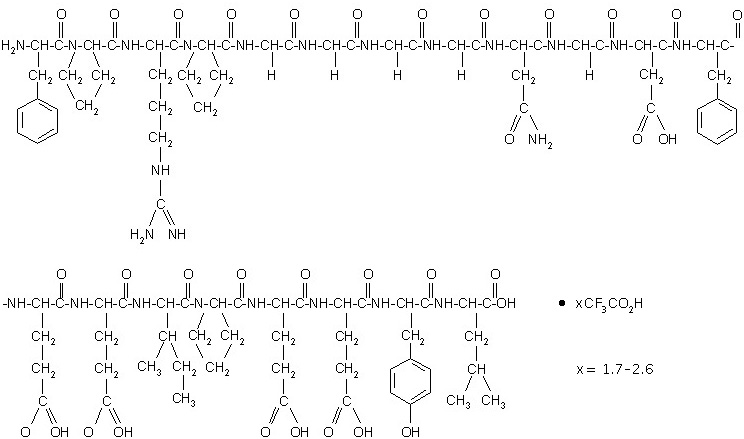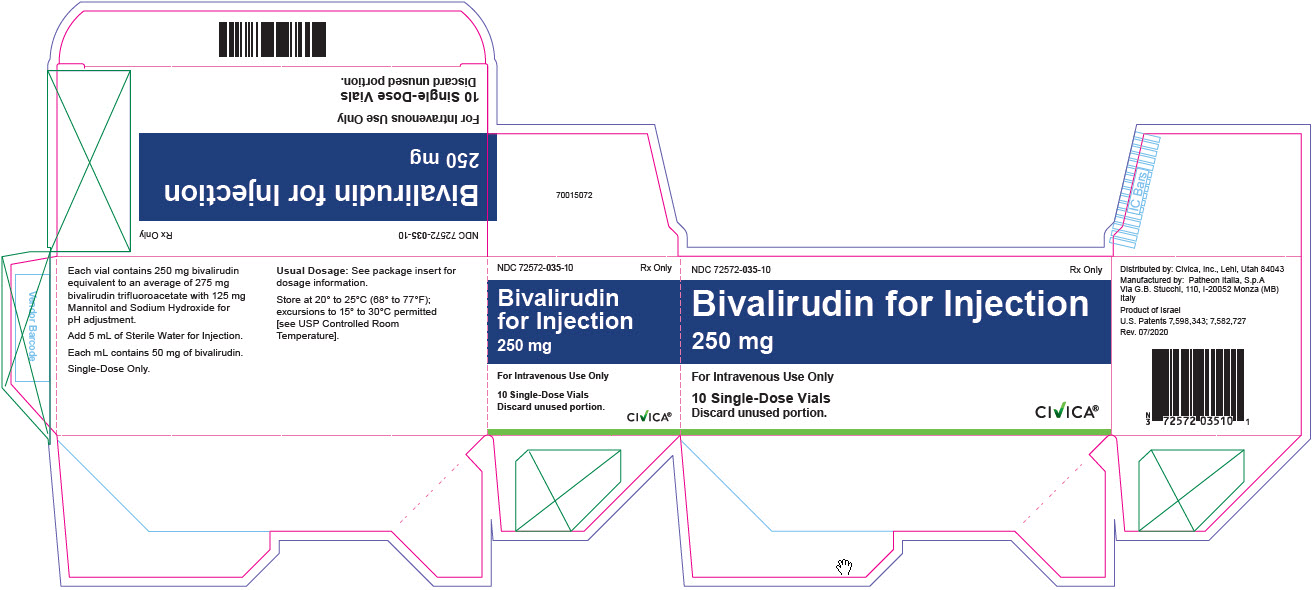 DRUG LABEL: bivalirudin
NDC: 72572-035 | Form: INJECTION, POWDER, LYOPHILIZED, FOR SOLUTION
Manufacturer: Civica, Inc.
Category: prescription | Type: HUMAN PRESCRIPTION DRUG LABEL
Date: 20250910

ACTIVE INGREDIENTS: BIVALIRUDIN 250 mg/1 1
INACTIVE INGREDIENTS: MANNITOL; SODIUM HYDROXIDE

HIGHLIGHTS OF PRESCRIBING INFORMATION

These highlights do not include all the information needed to use BIVALIRUDIN FOR INJECTION safely and effectively. See full prescribing information for BIVALIRUDIN FOR INJECTION.
BIVALIRUDIN for injection, for intravenous use
Initial U.S. Approval: 2000

1 INDICATIONS AND USAGE

Bivalirudin for injection is a direct thrombin inhibitor indicated for use as an anticoagulant in patients undergoing percutaneous coronary intervention (PCI) including patients with heparin-induced thrombocytopenia (HIT) or heparin-induced thrombocytopenia and thrombosis syndrome (HITTS).(1)

2 DOSAGE AND ADMINISTRATION

- The recommended dosage is a 0.75 mg/kg intravenous bolus dose followed immediately by a 1.75 mg/kg/h intravenous infusion for the duration of the procedure. Five minutes after the bolus dose has been administered, an activated clotting time (ACT) should be performed and an additional bolus dose of 0.3 mg/kg should be given if needed.
- Extending duration of infusion post-procedure up to 4 hours should be considered in patients with ST segment elevation MI (STEMI). (2.1)

3 DOSAGE FORMS AND STRENGTHS

For injection: 250 mg of bivalirudin as a lyophilized powder in a single dose vial for reconstitution. (3)

4 CONTRAINDICATIONS

- Active major bleeding (4)
- Hypersensitivity to bivalirudin or its components (4)

5 WARNINGS AND PRECAUTIONS

- Bleeding Events: Bivalirudin increases the risk of bleeding. (5.1, 6.1, 12.2)
- Acute Stent Thrombosis: Increased incidence of acute stent thrombosis in STEMI patients undergoing primary PCI. (2.1, 5.2)
- Thrombotic Risk with Coronary Artery Brachytherapy: An increased risk of thrombus formation, including fatal outcomes, in gamma brachytherapy. (5.3)

6 ADVERSE REACTIONS

Most common adverse reaction (>2%) was bleeding. (6.1)

To report SUSPECTED ADVERSE REACTIONS, contact Sandoz Inc. at 1-800-525-8747 or FDA at 1-800-FDA-1088 or www.fda.gov/medwatch.

7 DRUG INTERACTIONS

Heparin, warfarin, thrombolytics, or GPIs: Increased major bleeding risk with concomitant use. (7)

8 USE IN SPECIFIC POPULATIONS

- Geriatric patients: Increased bleeding risk possible. (8.5)
- Renal impairment: Reduce infusion dose and monitor ACT. (2.2, 8.6)

FULL PRESCRIBING INFORMATION

1 INDICATIONS AND USAGE

Bivalirudin for injection is indicated for use as an anticoagulant for use in patients undergoing percutaneous coronary intervention (PCI) including patients with heparin-induced thrombocytopenia and heparin-induced thrombocytopenia and thrombosis syndrome.

2 DOSAGE AND ADMINISTRATION

2.1 Recommended Dosage

Bivalirudin has been studied only in patients receiving concomitant aspirin.

The recommended dose of bivalirudin is an intravenous bolus dose of 0.75 mg/kg, followed immediately by an infusion of 1.75 mg/kg/h for the duration of the procedure. Five minutes after the bolus dose has been administered, an activated clotting time (ACT) should be performed and an additional bolus of 0.3 mg/kg should be given if needed.

Extended duration of infusion following PCI at 1.75 mg/kg/h for up to 4 hours post-procedure should be considered in patients with ST segment elevation MI (STEMI).

2.2 Dose Adjustment in Renal Impairment

Bolus Dose

No reduction in the bolus dose is needed for any degree of renal impairment.

Maintenance Infusion

In patients with creatinine clearance less than 30mL/min (by Cockcroft Gault equation), reduce the infusion rate to 1 mg/kg/h. Monitor anticoagulant status in patients with renal impairment.

In patients on hemodialysis, reduce the infusion rate to 0.25 mg/kg/h [see Use in Specific Populations (8.6), Clinical Pharmacology (12.3)].

2.3 Instructions for Preparation and Administration

Bivalirudin is intended for intravenous bolus injection and continuous infusion after reconstitution and dilution.
Preparation Instructions for Bolus Injection and Continuous Infusion
3. To each 250 mg vial, add 5 mL of Sterile Water for Injection, USP.
4. Gently swirl until all material is dissolved.
5. Withdraw and discard 5 mL from a 50 mL infusion bag containing 5% Dextrose in Water or 0.9% Sodium Chloride for Injection.
6. Add the contents of the reconstituted vial to the infusion bag containing 5% Dextrose in Water or 0.9% Sodium Chloride for Injection to yield a final concentration of 5 mg/mL (e.g., 1 vial in 50 mL; 2 vials in 100 mL; 5 vials in 250 mL).
7. Adjust the dose to be administered according to the patient’s weight (see Table 1).

Table 1: Dosing Table
Weight (kg) | Using 5 mg/mL Concentration
Weight (kg) | Bolus 0.75 mg/kg (mL) | Infusion 1.75 mg/kg/h (mL/h)
43-47 | 7 | 16
48-52 | 7.5 | 17.5
53-57 | 8 | 19
58-62 | 9 | 21
63-67 | 10 | 23
68-72 | 10.5 | 24.5
73-77 | 11 | 26
78-82 | 12 | 28
83-87 | 13 | 30
88-92 | 13.5 | 31.5
93-97 | 14 | 33
98-102 | 15 | 35
103-107 | 16 | 37
108-112 | 16.5 | 38.5
113-117 | 17 | 40
118-122 | 18 | 42
123-127 | 19 | 44
128-132 | 19.5 | 45.5
133-137 | 20 | 47
138-142 | 21 | 49
143-147 | 22 | 51
148-152 | 22.5 | 52.5

Drug Compatibilities

No incompatibilities have been observed with administration sets.

Do not administer the drugs listed in Table 2 in the same intravenous line with Bivalirudin.

Table 2: Drugs Not for Administration in the Same Intravenous Line with Bivalirudin

Alteplase

Amiodarone HCl

Amphotericin B

Chlorpromazine HCl

Diazepam

Dobutamine

Prochlorperazine Edisylate

Reteplase

Streptokinase

Vancomycin HCl

Parenteral drug products should be inspected visually for particulate matter and discoloration prior to administration. Preparations of bivalirudin containing particulate matter should not be used. Reconstituted material will be a clear to slightly opalescent, colorless to slightly yellow solution.

2.4 Storage after Reconstitution

Do not freeze reconstituted or diluted Bivalirudin. Reconstituted material may be stored at 2° to 8°C for up to 24 hours. Diluted bivalirudin with a concentration of between 0.5 mg/mL and 5 mg/mL is stable at room temperature for up to 24 hours. Discard any unused portion of reconstituted solution remaining in the vial.

3 DOSAGE FORMS AND STRENGTHS

For injection: 250 mg of bivalirudin as a lyophilized powder in a single dose vial for reconstitution. Each vial contains 250 mg of bivalirudin equivalent to an average of 275 mg bivalirudin trifluoroacetate*.

*The range of bivalirudin trifluoroacetate is 270 to 280 mg based on a range of trifluoroacetic acid composition of 1.7 to 2.6 equivalents.

4 CONTRAINDICATIONS

Bivalirudin is contraindicated in patients with:

- Active major bleeding;
- Hypersensitivity (e.g., anaphylaxis) to bivalirudin or its components [see Adverse Reactions (6.1)].

5 WARNINGS AND PRECAUTIONS

5.1 Bleeding Events

Bivalirudin increases the risk of bleeding [see Adverse Reactions (6.1)]. An unexplained fall in blood pressure or hematocrit should lead to serious consideration of a hemorrhagic event and cessation of bivalirudin administration. Monitor patients receiving bivalirudin for signs and symptoms of bleeding. Monitor patients with disease states associated with an increased risk of bleeding more frequently for bleeding.

5.2 Acute Stent Thrombosis in Patients with STEMI Undergoing PCI

Acute stent thrombosis (AST) (less than 4 hours) has been observed at a greater frequency in bivalirudin treated patients (1.2%, 36/2889) compared to heparin treated patients (0.2%, 6/2911) with STEMI undergoing primary PCI. Among patients who experienced an AST, one fatality (0.03%) occurred in a bivalirudin treated patient and one fatality (0.03%) in a heparin treated patient. These patients have been managed by Target Vessel Revascularization (TVR). Patients should remain for at least 24 hours in a facility capable of managing ischemic complications and should be carefully monitored following primary PCI for signs and symptoms consistent with myocardial ischemia.

5.3 Thrombotic Risk with Coronary Artery Brachytherapy

An increased risk of thrombus formation, including fatal outcomes, has been associated with the use of bivalirudin in gamma brachytherapy.

If a decision is made to use bivalirudin during brachytherapy procedures, maintain meticulous catheter technique, with frequent aspiration and flushing, paying special attention to minimizing conditions of stasis within the catheter or vessels [see Adverse Reactions (6.3)].

6 ADVERSE REACTIONS

6.1 Clinical Trials Experience

Because clinical trials are conducted under widely varying conditions, adverse reaction rates observed in the clinical trials of a drug cannot be directly compared to rates in the clinical trials of another drug and may not reflect the rates observed in practice.

In the BAT trials, 79 of the 2161 (3.7%) patients undergoing PCI for treatment of unstable angina and randomized to bivalirudin experienced major bleeding events, which consisted of intracranial bleeding, retroperitoneal bleeding, and clinically overt bleeding with a decrease in hemoglobin greater than 3 g/dL or leading to a transfusion of greater than 2 units of blood.

6.2 Immunogenicity

As with all peptides, there is potential for immunogenicity. The detection of antibody formation is highly dependent on the sensitivity and specificity of the assay. Additionally, the observed incidence of antibody (including neutralizing antibody) positivity in an assay may be influenced by several factors including assay methodology, sample handling, timing of sample collection, concomitant medications, and underlying disease. For these reasons, comparison of the incidence of antibodies to bivalirudin in the studies described below with the incidence of antibodies in other studies or to other products may be misleading.

In in vitro studies, bivalirudin exhibited no platelet aggregation response against sera from patients with a history of HIT/HITTS.

Among 494 subjects who received bivalirudin in clinical trials and were tested for antibodies, 2 subjects had treatment-emergent positive bivalirudin antibody tests. Neither subject demonstrated clinical evidence of allergic or anaphylactic reactions and repeat testing was not performed. Nine additional patients who had initial positive tests were negative on repeat testing.

6.3 Postmarketing Experience

Because postmarketing adverse reactions are reported voluntarily from a population of uncertain size, it is not always possible to reliably estimate their frequency or establish a causal relationship to drug exposure.

The following adverse reactions have been identified during post approval use of bivalirudin: fatal bleeding; hypersensitivity and allergic reactions including reports of anaphylaxis; lack of anticoagulant effect; thrombus formation during PCI with and without intracoronary brachytherapy, including reports of fatal outcomes; pulmonary hemorrhage; cardiac tamponade; and INR increased.

7 DRUG INTERACTIONS

In clinical trials in patients undergoing PCI/ percutaneous transluminal coronary angioplasty (PTCA), coadministration of bivalirudin with heparin, warfarin, thrombolytics, or GPIs was associated with increased risks of major bleeding events compared to patients not receiving these concomitant medications.

8 USE IN SPECIFIC POPULATIONS

8.1 Pregnancy

Risk Summary

There are no data available on use of bivalirudin in pregnant women to inform a drug-associated risk of adverse developmental outcomes. Reproduction studies in rats and rabbits administered subcutaneously doses up to 1.6 times and 3.2 times the maximum recommended human dose (MRHD) of 15 mg/kg/day based on body surface area (BSA) during organogenesis, respectively, revealed no evidence of fetal harm.

All pregnancies have a background risk of birth defect, loss, or other adverse outcomes. The estimated background risk of major birth defects and miscarriage for the indicated population is unknown. In the U.S. general population, the estimated background risk of major birth defects and miscarriage in clinically recognized pregnancies is 2 to 4% and 15 to 20%, respectively.

Data

Animal Data

Reproductive studies have been performed in rats at subcutaneous doses up to 150 mg/kg/day (1.6 times the maximum recommended human dose based on body surface area) and rabbits at subcutaneous doses up to 150 mg/kg/day (3.2 times the maximum recommended human dose based on body surface area). These studies revealed no harm to the fetus attributable to bivalirudin. At 500 mg/kg/day (equivalent to 5.4 times the maximum recommended human dose based on body surface area) subcutaneously, litter sizes and live fetuses in rats were reduced. Fetal skeletal variations were also noted. Some of these changes could be attributed to maternal toxicity observed at high doses.

There is no study covering the perinatal period because of the potential complications of drug-induced hemorrhage during delivery.

8.2 Lactation

Risk Summary

It is not known whether bivalirudin is present in human milk. No data are available on the effects

on the breastfed child or on milk production.

Bivalirudin was administered to lactating rats in reproduction studies (see Data). The developmental and health benefits of breastfeeding should be considered along with the mother’s clinical need for bivalirudin and any potential adverse effects on the breastfed child from bivalirudin or from the underlying maternal condition.

Data

Animal Data

Reproduction studies conducted in lactating female rats dosed subcutaneously daily with bivalirudin at doses up to 150 mg/kg/day (1.6 times the maximum recommended human dose, based on body surface area) from day 2 through day 20 of lactation revealed no adverse developmental outcomes to the pups.

8.4 Pediatric Use

The safety and effectiveness of bivalirudin in pediatric patients have not been established.

8.5 Geriatric Use

In studies of patients undergoing PCI, 44% were ≥65 years of age and 12% of patients were ≥75 years old. Elderly patients experienced more bleeding events than younger patients.

8.6 Renal Impairment

The disposition of bivalirudin was studied in PTCA patients with mild, moderate and severe renal impairment. The clearance of bivalirudin was reduced approximately 21% in patients with moderate and severe renal impairment and was reduced approximately 70% in dialysis-dependent patients [see Clinical Pharmacology (12.3)]. Reduce the infusion dose of bivalirudin and monitor the anticoagulant status more frequently in patients with renal impairment creatinine clearance less than 30 mL/min (by Cockcroft Gault equation) [see Dosage and Administration (2.2)].

10 OVERDOSAGE

Cases of overdose of up to 10 times the recommended bolus or continuous infusion dose of bivalirudin have been reported in clinical trials and in postmarketing reports. A number of the reported overdoses were due to failure to adjust the infusion dose of bivalirudin in persons with renal dysfunction including persons on hemodialysis [see Dosage and Administration (2.2)]. Bleeding, as well as deaths due to hemorrhage, have been observed in some reports of overdose. In cases of suspected overdosage, discontinue bivalirudin immediately and monitor the patient closely for signs of bleeding. There is no known antidote to bivalirudin. Bivalirudin is hemodialyzable [see Clinical Pharmacology (12.3)].

11 DESCRIPTION

Bivalirudin for injection contains bivalirudin, which is a specific and reversible direct thrombin inhibitor. Bivalirudin is a synthetic, 20 amino acid peptide, with the chemical name of D-phenylalanyl-L-prolyl-L-arginyl-L-prolyl-glycyl-glycyl-glycyl-glycyl-L-asparagyl-glycyl-L-aspartyl-L-phenylalanyl-L-glutamyl-L-glutamyl-L-isoleucyl-L-prolyl-L-glutamyl-L-glutamyl-L-tyrosyl-L-leucine. The active pharmaceutical ingredient is in the form of bivalirudin trifluoroacetate as a white to off-white powder. The chemical name for bivalirudin trifluoroacetate is D-phenylalanyl-L-prolyl-L-arginyl-L-prolyl-glycyl-glycyl-glycyl-glycyl-L-asparagyl-glycyl-L-aspartyl-L-phenylalanyl-L-glutamyl-L-glutamyl-L-isoleucyl-L-prolyl-L-glutamyl-L-glutamyl-L-tyrosyl-L-leucine trifluoroacetate (Figure 1). The molecular weight of bivalirudin is 2180 daltons (anhydrous free base peptide).

Figure 1: Structure Formula for Bivalirudin Trifluoroacetate

Bivalirudin for injection is supplied as a sterile white lyophilized cake, in single-dose vials. Each vial contains 250 mg bivalirudin, equivalent to an average of 275 mg of bivalirudin trifluoroacetate*, 125 mg mannitol, and sodium hydroxide to adjust the pH to 5-6 (equivalent of approximately 12.5 mg sodium). When reconstituted with Sterile Water for Injection, the product yields a clear to opalescent, colorless to slightly yellow solution, pH 5-6.

*The range of bivalirudin trifluoroacetate is 270 mg to 280 mg based on a range of trifluoroacetic acid composition of 1.7 to 2.6 equivalents.

12 CLINICAL PHARMACOLOGY

12.1 Mechanism of Action

Bivalirudin directly inhibits thrombin by specifically binding both to the catalytic site and to the anion-binding exosite of circulating and clot-bound thrombin. Thrombin is a serine proteinase that plays a central role in the thrombotic process, acting to cleave fibrinogen into fibrin monomers and to activate Factor XIII to Factor XIIIa, allowing fibrin to develop a covalently cross-linked framework, which stabilizes the thrombus; thrombin also activates Factors V and VIII, promoting further thrombin generation, and activates platelets, stimulating aggregation and granule release. The binding of bivalirudin to thrombin is reversible as thrombin slowly cleaves the bivalirudin-Arg3-Pro4 bond, resulting in recovery of thrombin active site functions.

In in vitro studies, bivalirudin inhibited both soluble (free) and clot-bound thrombin, was not neutralized by products of the platelet release reaction, and prolonged the activated partial thromboplastin time (aPTT), thrombin time (TT), and prothrombin time (PT) of normal human plasma in a concentration-dependent manner. The clinical relevance of these findings is unknown.

12.2 Pharmacodynamics

In healthy volunteers and patients (with ≥70% vessel occlusion undergoing routine PTCA), bivalirudin exhibited dose- and concentration-dependent anticoagulant activity as evidenced by prolongation of the ACT, aPTT, PT, and TT. Intravenous administration of bivalirudin produces an immediate anticoagulant effect. Coagulation times return to baseline approximately 1 hour following cessation of bivalirudin administration. Bivalirudin also increases INR. Therefore, INR measurements made in bivalirudin treated patients may not be useful for determining the appropriate dose of warfarin.

In 291 patients with ≥70% vessel occlusion undergoing routine PTCA, a positive correlation was observed between the dose of bivalirudin and the proportion of patients achieving ACT values of 300 sec or 350 sec. At a bivalirudin dose of 1 mg/kg IV bolus plus 2.5 mg/kg/h IV infusion for 4 hours, followed by 0.2 mg/kg/h, all patients reached maximal ACT values greater than 300 sec.

12.3 Pharmacokinetics

Bivalirudin exhibits linear pharmacokinetics following IV administration to patients undergoing PTCA. In these patients, a mean steady state bivalirudin concentration of 12.3 ± 1.7 mcg/mL is achieved following an IV bolus of 1 mg/kg and a 4-hour 2.5 mg/kg/h IV infusion.

Distribution

Bivalirudin does not bind to plasma proteins (other than thrombin) or to red blood cells.

Elimination

Bivalirudin has a half-life of 25 minutes in PTCA patients with normal renal function. The total body clearance of bivalirudin in PTCA patients with normal renal function is 3.4 mL/min/kg.

Metabolism

Bivalirudin is metabolized by proteolytic cleavage.

Excretion

Bivalirudin undergoes glomerular filtration. Tubular secretion and tubular reabsorption are also implicated in the excretion of bivalirudin, although the extent is unknown.

Specific Populations

Patients with Renal Impairment

Total body clearance was similar for PTCA patients with normal renal function and with mild renal impairment. Clearance was reduced by 21% in patients with moderate and severe renal impairment with a half-life of 34 and 57 minutes, respectively. In dialysis patients, clearance was reduced by 70%, with a half-life of 3.5 hours. Approximately 25% bivalirudin is cleared by hemodialysis.

13 NONCLINICAL TOXICOLOGY

13.1 Carcinogenesis, Mutagenesis, Impairment of Fertility

No long-term studies in animals have been performed to evaluate the carcinogenic potential of bivalirudin. Bivalirudin displayed no genotoxic potential in the in vitro bacterial cell reverse mutation assay (Ames test), the in vitro Chinese hamster ovary cell forward gene mutation test (CHO/HGPRT), the in vitro human lymphocyte chromosomal aberration assay, the in vitro rat hepatocyte unscheduled DNA synthesis (UDS) assay, and the in vivo rat micronucleus assay. Fertility and general reproductive performance in rats were unaffected by subcutaneous doses of bivalirudin up to 150 mg/kg/day, about 1.6 times the dose on a body surface area basis (mg/m^2) of a 50 kg person given the maximum recommended dose of 15 mg/kg/day.

14 CLINICAL STUDIES

Bivalirudin Angioplasty Trial (BAT)

In the BAT studies, patients with unstable angina undergoing PCI were randomized 1:1 to a 1 mg/kg bolus of bivalirudin and then 2.5 mg/kg/h for four hours and then 0.2 mg/kg/h for 14 to 20 hours or to 175 IU/kg bolus of heparin followed by an 18 to 24 hour infusion of 15 IU/kg/h infusion. Additional heparin but not bivalirudin could be administered for ACT less than 350 seconds. The studies were designed to demonstrate the superiority of bivalirudin to heparin on the occurrence of any of the following during hospitalization up to seven days of death, MI, abrupt closure of dilated vessel, or clinical deterioration requiring revascularization or placement of an aortic balloon pump.

The 4312 subjects ranged in age from 29 to 90 (median 63) years. 68% were male, and 91% were Caucasian. Median weight was 80 kg (39 to 120 kg). 741 (17%) subjects had post-MI angina. Twenty-three percent of patients were treated with heparin within one hour prior to randomization.

The studies did not demonstrate that bivalirudin was statistically superior to heparin for reducing the risk of death, MI, abrupt closure of the dilated vessel, or clinical deterioration requiring revascularization or placement of an aortic balloon pump, but the occurrence of these events was similar in both treatment groups. Study outcomes are shown in Table 3.

Table 3: Incidences of In-hospital Endpoints in BAT Trial

Endpoint | Bivalirudin (n=2161) | HEPARIN (n=2151)
Primary Endpoint [A composite of death or MI or clinical deterioration of cardiac origin requiring revascularization or placement of an aortic balloon pump or angiographic evidence of abrupt vessel closure.] | 7.9% | 9.3%
Death, MI, revascularization | 6.2% | 7.9%
Death | 0.2% | 0.2%
MI | 3.3% | 4.2%

AT-BAT Trial (NCT# 00043940)

This was a single-arm open-label study in which 51 patients with heparin-induced thrombocytopenia (HIT) or heparin induced thrombocytopenia and thrombosis syndrome (HITTS) underwent PCI. The majority of patients achieved adequate ACT at the time of device activation and no major bleeding was reported. Evidence for the diagnosis of HIT/HITTS was based on a clinical history of a decrease of platelets in patients after heparin administration [new diagnosis or history of clinically suspected or objectively documented HIT/HITTS defined as either: 1) HIT: positive heparin-induced platelet aggregation (HIPA) or other functional assay where the platelet count has decreased to less than 100,000/mL (minimum 30% from prior to heparin), or has decreased to less than 150,000/mL (minimum 40% from prior to heparin), or has decreased as above within hours of receiving heparin in a patient with a recent, previous exposure to heparin; 2) HITTS: thrombocytopenia as above plus arterial or venous thrombosis diagnosed by physician examination/laboratory and/or appropriate imaging studies]. Patients ranged in age from 48 to 89 years (median 70); weight ranged from 42 to 123 kg (median 76); 50% were male and 50% were female. Bivalirudin was administered as either 1 mg/kg bolus followed by 2.5 mg/kg/h (high dose in 28 patients) or 0.75 mg/kg bolus followed by a 1.75 mg/kg/h infusion (lower dose in 25 patients) for up to 4 hours. Ninety-eight percent of patients received aspirin, 86% received

clopidogrel and 19% received GPIs.

The median ACT values at the time of device activation were 379 sec (high dose) and 317 sec (lower dose). Following the procedure, 48 of the 51 patients (94%) had TIMI grade 3 flow and stenosis less than 50%. One patient died during a bradycardic episode 46 hours after successful PCI, another patient required surgical revascularization, and one patient experienced no flow requiring a temporary intra-aortic balloon.

Two of the fifty-one patients with the diagnosis of HIT/HITTS developed thrombocytopenia after receiving bivalirudin and GPIs.

16 HOW SUPPLIED/STORAGE AND HANDLING

16.1 How Supplied

Bivalirudin for injection is supplied as a sterile, lyophilized powder in single-dose, glass vials. Each vial contains 250 mg of bivalirudin equivalent to an average of 275 mg of bivalirudin trifluoroacetate*.

*The range of bivalirudin trifluoroacetate is 270 to 280 mg based on a range of trifluoroacetic

acid composition of 1.7 to 2.6 equivalents.

NDC 72572-035-10 – Package of 10 – 250 mg Single-Dose Vials

16.2 Storage

Store bivalirudin for injection dosage units at 20° to 25°C (68° to 77°F); excursions to 15° to 30°C permitted [see USP Controlled Room Temperature].

17 PATIENT COUNSELING INFORMATION

Advise patients to watch carefully for any signs of bleeding or bruising and to report these to their health care provider when they occur.

Distributed by: Civica, Inc., Lehi, Utah 84043

Manufactured by: Patheon Italia, S.p.A.

Via G.B. Stucchi, 110

I-20052 Monza (MB), Italy

U.S. Patents 7,598,343; 7,582,727

PRINCIPAL DISPLAY PANEL

NDC 72572-035-10

Bivalirudin for Injection

250 mg

Rx Only

For Intravenous Use Only

10 Single-Dose Vials

Discard unused portion.